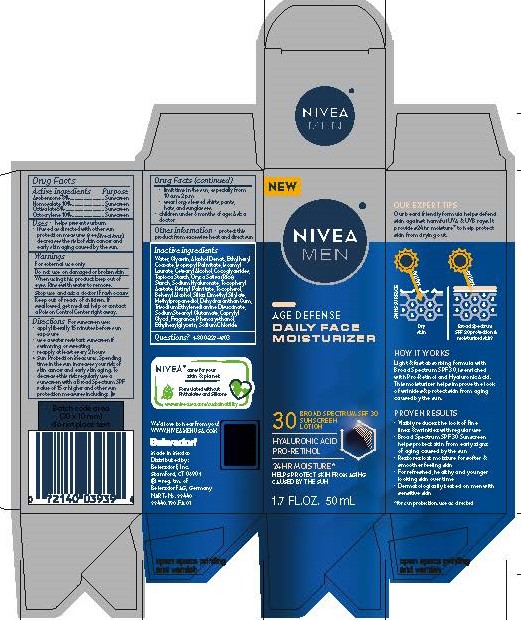 DRUG LABEL: NIVEA MEN Age Defense Face Moisturizer
NDC: 10356-580 | Form: LOTION
Manufacturer: Beiersdorf Inc
Category: otc | Type: HUMAN OTC DRUG LABEL
Date: 20251231

ACTIVE INGREDIENTS: HOMOSALATE 10 g/100 g; OCTOCRYLENE 10 g/100 g; AVOBENZONE 3 g/100 g; OCTISALATE 5 g/100 g
INACTIVE INGREDIENTS: TAPIOCA STARCH; RETINYL PALMITATE; BEHENYL ALCOHOL; ALPHA-TOCOPHEROL ACETATE; ISOPROPYL PALMITATE; ETHYLHEXYL COCOATE; COCOGLYCERIDES; SODIUM HYALURONATE; SODIUM CHLORIDE; ALCOHOL; ETHYLHEXYLGLYCERIN; SODIUM STEAROYL GLUTAMATE; CETOSTEARYL ALCOHOL; WATER; GLYCERIN; SILICA DIMETHYL SILYLATE; PHENOXYETHANOL; ISOAMYL LAURATE; METHYLPROPANEDIOL; TRISODIUM ETHYLENEDIAMINE DISUCCINATE; CAPRYLYL GLYCOL; ORYZA SATIVA (RICE) STARCH; DEHYDROXANTHAN GUM

NIVEA MEN Age Defense Face Moisturizer

Active ingredients

Avobenzone 3%

Homosalate 10%

Octisalate 5%

Octocrylene 10%

Purpose

Sunscreens

Uses
• helps prevent sunburn
• if used as directed with other sun protection measures (see Directions),
decreases the risk of skin cancer and early skin aging caused by the sun

Warnings
For external use only

.

Do not use on damaged or broken skin.

When using this product keep out of eyes. Rinse with water to remove.

Stop use and ask a doctor if rash occurs

Keep out of reach of children. If swallowed, get medical help or contact a Poison Control Center right away.

Directions

For sunscreen use:
• apply liberally 15 minutes before sun exposure
• use a water resistant sunscreen if swimming or sweating
• reapply at least every 2 hours
• children under 6 months of age: Ask a doctor
• Sun Protection Measures. Spending time in the sun increases your risk of skin cancer and
early skin aging. To decrease this risk, regularly use a sunscreen with a Broad Spectrum SPF
value of 15 or higher, and other sun protection measures including:
• limit time in the sun, especially from 10 a.m. - 2 p.m.
• wear long-sleeved shirts, pants, hats, and sunglasses.
• children under 6 months of age: Ask a doctor.

Other information

protect this product from excessive heat and direct sun

Inactive ingredients

Water, Glycerin, Alcohol Denat., Ethylhexyl Cocoate, Isopropyl Palmitate, Isoamyl Laurate, Cetearyl Alcohol, Cocoglycerides, Tapioca Starch, Oryza Sativa (Rice) Starch, Sodium Hyaluronate, Tocopheryl Acetate, Retinyl Palmitate, Tocopherol, Behenyl Alcohol, Silica Dimethyl Silylate, Methylpropanediol, Dehydroxanthan Gum, Trisodium Ethylenediamine Disuccinate, Sodium Stearoyl Glutamate, Caprylyl Glycol, Fragrance, Phenoxyethanol, Ethylhexylglycerin, Sodium Chloride

PACKAGE LABEL

NIVEA MEN

Age Defense Daily Face Moisturizer

30

Broad spectrum SPF 30

Sunscreen Lotion

Hyaluronic acid

Pro-Retinol

24 hour moisture*

Helps protect skin from aging caused by the sun

*for sun protection use as directed